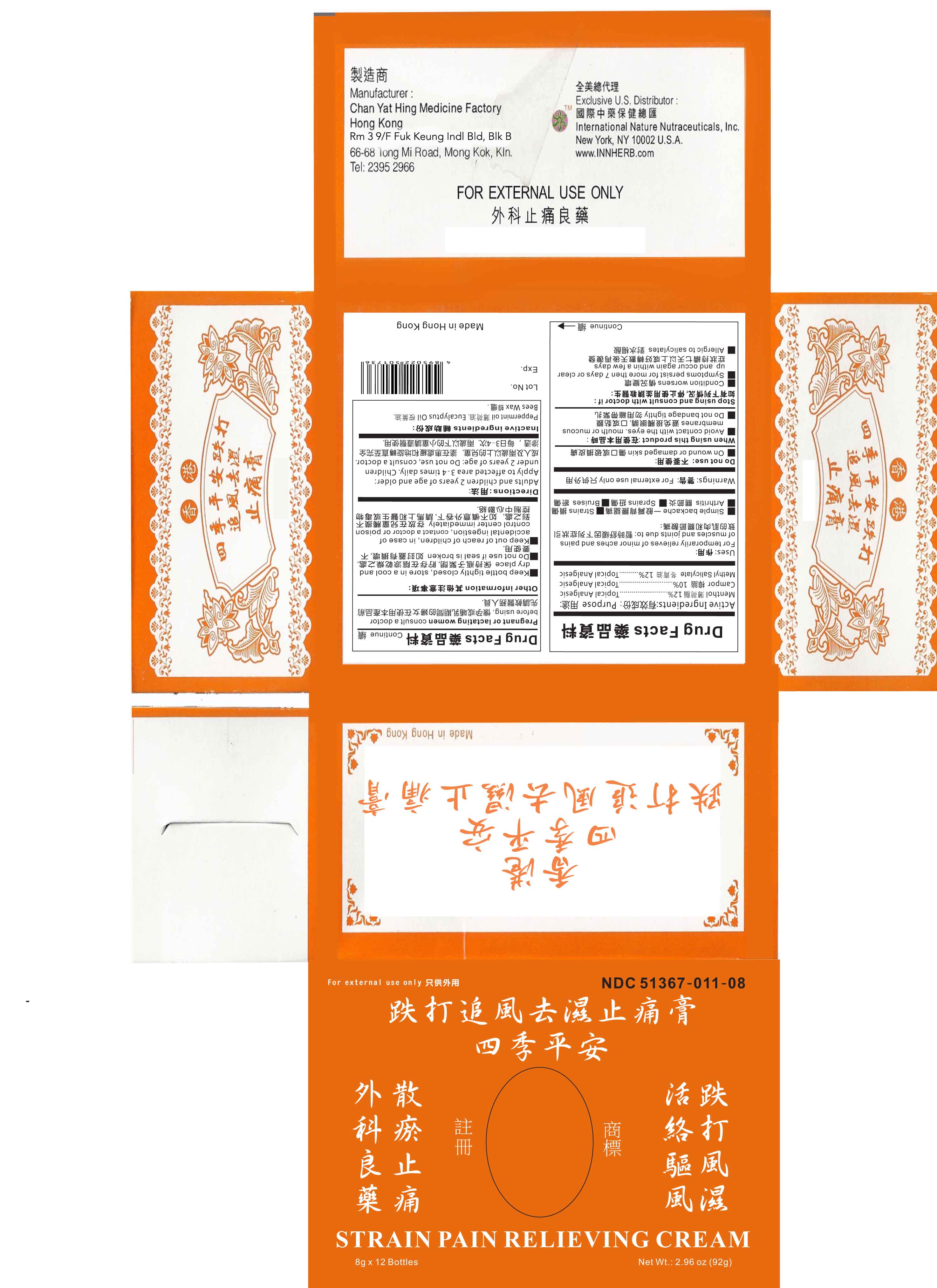 DRUG LABEL: Strain Pain Relieving Cream
NDC: 51367-011 | Form: CREAM
Manufacturer: International Nature Nutraceuticals
Category: otc | Type: HUMAN OTC DRUG LABEL
Date: 20130804

ACTIVE INGREDIENTS: MENTHOL 854.4 mg/1 1; CAMPHOR (NATURAL) 796.8 mg/1 1; METHYL SALICYLATE 1.13 g/1 1
INACTIVE INGREDIENTS: PEPPERMINT OIL; EUCALYPTUS OIL; YELLOW WAX

Drug Facts

Active Ingredients

Menthol- 12%

Camphor- 10%

Methyl Salicylate- 12%

Uses

For temporarily relieves of minor aches and pains of muscles and joints due to:

- simple backache
- strains
- arthirtis
- sprains
- bruises

Warnings

For external use only

Do not use

On wound or damaged skin

When using this product

Avoid contact with the eyes, mouth or mucous membranes

Do not bandage tightly

Stop using and consult with doctor if

Condition worsens

Symptoms persist for more than 7 days or clear up and occur again within a few days

Allergic to salicylates

Pregnant or lactating women

Consult a doctor before using

Other information

Keep bottle tightly closed, store in a cool and dry place

Do not use if seal is broken

In case of accidental ingestion, contact a doctor or poison control center immediately

Directions

Adults and cildren 2 years of age and older: apply to affected area 3-4 times daily

Children under 2 years of age: do not use, consult a doctor

Inactive Ingredients

Peppermint oil, eucalyptus oil, bees wax